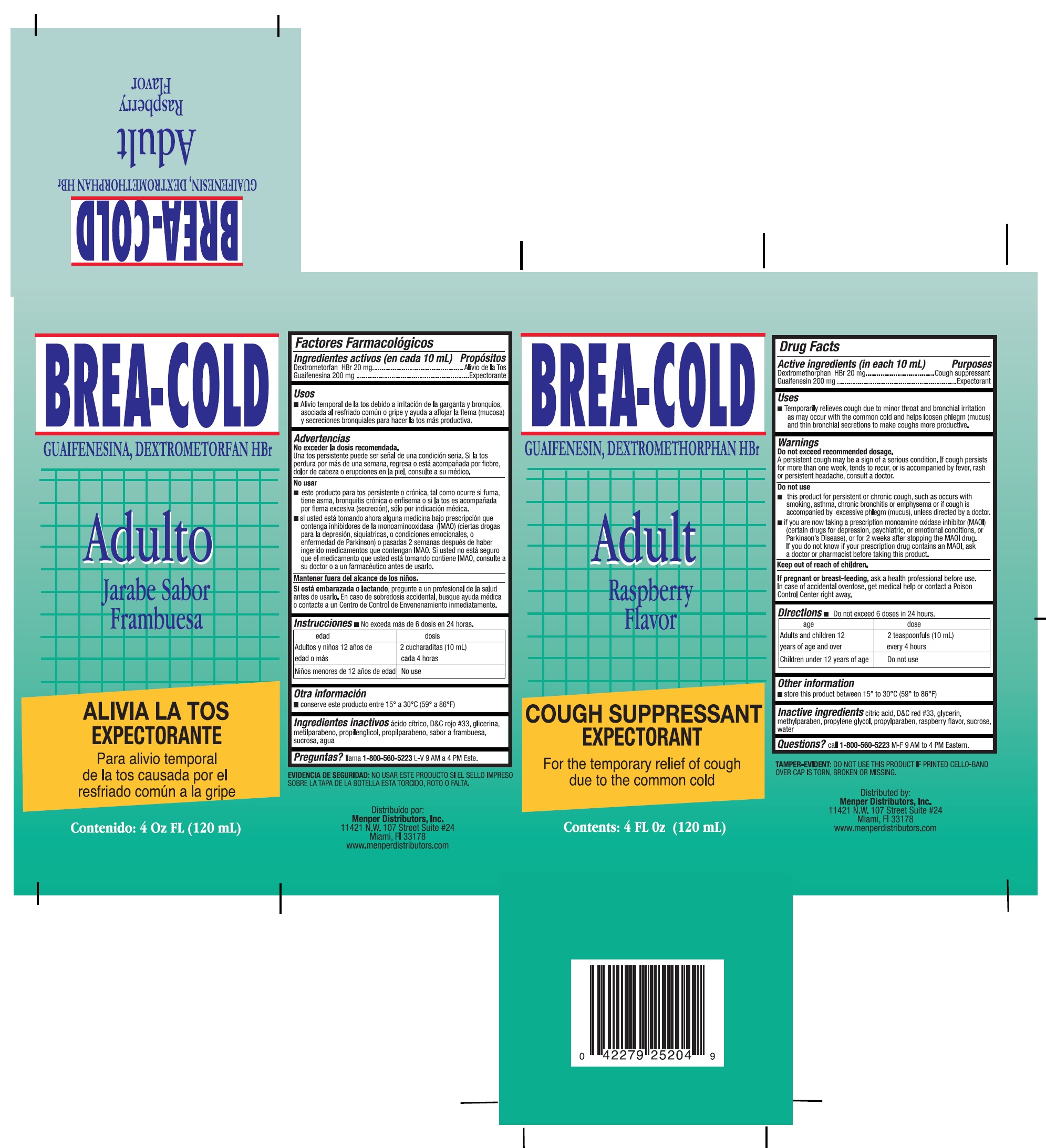 DRUG LABEL: Breacold Adult
NDC: 53145-040 | Form: LIQUID
Manufacturer: Menper Distributors, Inc.
Category: otc | Type: HUMAN OTC DRUG LABEL
Date: 20220218

ACTIVE INGREDIENTS: GUAIFENESIN 200 mg/10 mL; DEXTROMETHORPHAN HYDROBROMIDE 20 mg/10 mL
INACTIVE INGREDIENTS: CITRIC ACID ACETATE; GLYCERIN; PROPYLENE GLYCOL; METHYLPARABEN; PROPYLPARABEN; D&C RED NO. 33; SUCROSE; WATER; RASPBERRY

Active ingredients (in each 10mL tsp)

Guaifenesin 200 mg………………………………Expectorant

Dextromethorphan HBr 20 mg…………………….Cough suppressant

Purpose

Expectorant

Cough Suppressant

Uses

Temporarily relieves cough due to minor throat ands bronchial irritation as may occur with the common cold and helps loosen phlegm (mucus) and thin bronchial secretions to make coughs more productive.

Do not exceed recommended dosage.

A persistent cough may be a sign of a serious condition. If cough persists for more than one week, tends to recur, or is accompanied by fever, rash or persistent headache, consult a doctor.

Do not use:

- this product for persistent or chronic cough, such as occurs with smoking, asthma, chronic bronchitis, or emphysema, or where cough is accompanied by excessive phlegm (mucus) unless directed by a doctor.
- if you are now taking a prescription monoamine oxidase inhibitor (MAOI) (certain drugs for depression, psychiatric or emotional conditions, or Parkinson’s disease), or for 2 weeks after stopping the MAOI drug. If you do not know if your prescription drug contains an MAOI, ask a doctor or pharmacist before taking this product.

Keep out of reach of children.

If pregnant or breast-feeding

ask a health professional before use. In case of accidental overdose, get medical help or contact a Poison Control Center right away.

Directions: Do not exceed 6 doses in 24 hours.

Age | Dose
Adults and children 12 years of age and over | 2 teaspoonfuls (10 mL) every 4 hours
Children under 12 years of age | Do not use

Other information

- Store this product between 15°-30°C (59°-86°F)

Inactive ingredients

Citric acid, D&C red #33, glycerin, methylparaben, propylene glycol, propylparaben,raspberry flavor, sucrose, water